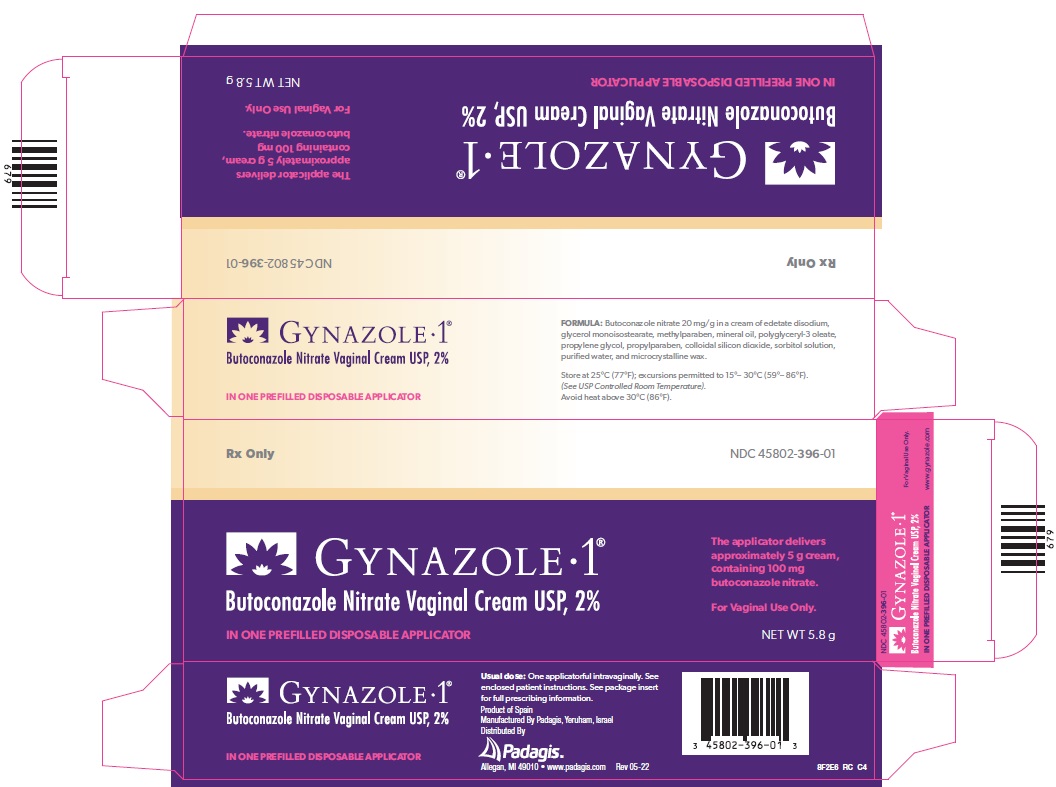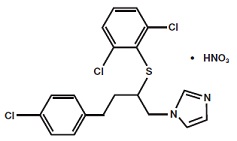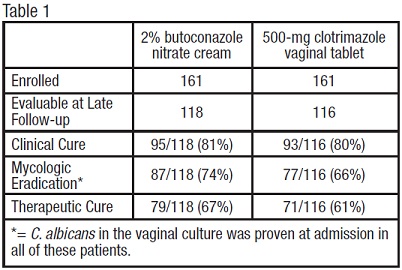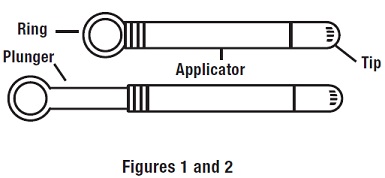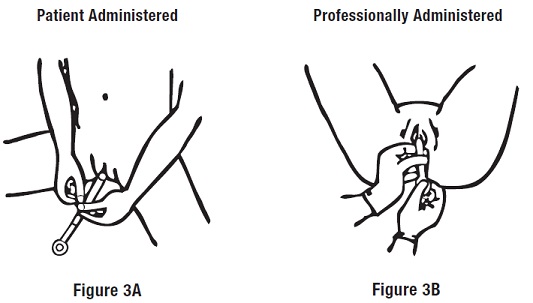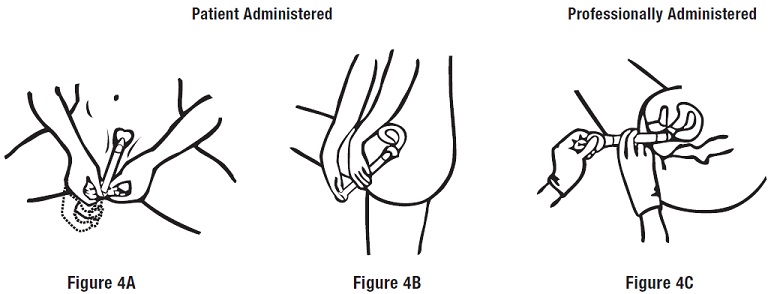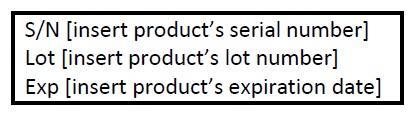 DRUG LABEL: gynazole 1
NDC: 45802-396 | Form: CREAM
Manufacturer: Padagis Israel Pharmaceuticals Ltd
Category: prescription | Type: HUMAN PRESCRIPTION DRUG LABEL
Date: 20230601

ACTIVE INGREDIENTS: BUTOCONAZOLE NITRATE 100 mg/5 g
INACTIVE INGREDIENTS: EDETATE DISODIUM; GLYCERYL ISOSTEARATE; METHYLPARABEN; MINERAL OIL; POLYGLYCERYL-3 OLEATE; PROPYLENE GLYCOL; PROPYLPARABEN; SILICON DIOXIDE; SORBITOL; WATER; MICROCRYSTALLINE WAX

GYNAZOLE•1®
Butoconazole Nitrate Vaginal Cream USP, 2%
IN ONE PREFILLED DISPOSABLE APPLICATOR
For Vaginal Use Only.
Rx Only

DESCRIPTION

GYNAZOLE • 1® Butoconazole Nitrate Vaginal Cream USP, 2% contains butoconazole nitrate 2%, an imidazole derivative with antifungal activity. Its chemical name is (±)-1-[4-(p-chlorophenyl)-2- [(2,6-dichlorophenyl) thio]butyl] imidazole mononitrate, and it has the following chemical structure:

Butoconazole nitrate is a white to off-white crystalline powder with a molecular weight of 474.79. It is sparingly soluble in methanol; slightly soluble in chloroform, methylene chloride, acetone, and ethanol; very slightly soluble in ethyl acetate; and practically insoluble in water. It melts at about 159°C with decomposition.

GYNAZOLE • 1® Butoconazole Nitrate Vaginal Cream USP, 2% contains 2% butoconazole nitrate in a cream of edetate disodium, glyceryl monoisostearate, methylparaben, mineral oil, polyglyceryl-3 oleate, propylene glycol, propylparaben, colloidal silicon dioxide, sorbitol solution, purified water, and microcrystalline wax.

CLINICAL PHARMACOLOGY

Following vaginal administration of butoconazole nitrate vaginal cream, 2% to 3 women, 1.7% (range 1.3-2.2%) of the dose was absorbed on average. Peak plasma levels (13.6-18.6 ng radioequivalents/mL of plasma) of the drug and its metabolites are attained between 12 and 24 hours after vaginal administration.

Microbiology -

The exact mechanism of the antifungal action of butoconazole nitrate is unknown; however, it is presumed to function as other imidazole derivatives via inhibition of steroid synthesis. Imidazoles generally inhibit the conversion of lanosterol to ergosterol, resulting in a change in fungal cell membrane lipid composition. This structural change alters cell permeability and, ultimately, results in the osmotic disruption or growth inhibition of the fungal cell.

Butoconazole nitrate is an imidazole derivative that has fungicidal activity in vitro against Candida spp. and has been demonstrated to be clinically effective against vaginal infections due to Candida albicans. Candida albicans has been identified as the predominant species responsible for vulvovaginal candidiasis.

INDICATIONS AND USAGE

GYNAZOLE • 1® Butoconazole Nitrate Vaginal Cream USP, 2% is indicated for the local treatment of vulvovaginal candidiasis (infections caused by Candida). The diagnosis should be confirmed by KOH smears and/or cultures (see CLINICAL STUDIES).

Note: GYNAZOLE • 1® Butoconazole Nitrate Vaginal Cream USP, 2% is safe and effective in non-pregnant women; however, the safety and effectiveness of this product in pregnant women has not been established (see PRECAUTIONS - Pregnancy).

CONTRAINDICATIONS

GYNAZOLE • 1® Butoconazole Nitrate Vaginal Cream USP, 2% is contraindicated in patients with a history of hypersensitivity to any of the components of the product.

CLINICAL STUDIES

Vulvovaginal Candidiasis: Two studies were conducted that compared 2% butoconazole nitrate cream with clotrimazole tablets. There were 322 enrolled patients, 161 received 2.0% butoconazole vaginal cream and 161 patients inserted the 500-mg clotrimazole vaginal tablet. At the second follow-up visit (30 days post-therapy), 118 patients in the butoconazole group and 116 in the clotrimazole group were evaluable for efficacy analysis, respectively. All of these patients had infection caused by Candida albicans.

The efficacy of the study drugs was assessed by evaluating clinical, mycologic and therapeutic cure rates, which are summarized in Table 1.

The therapeutic cure was defined as complete resolution of signs and symptoms of vaginal candidiasis (clinical cure) along with a negative KOH examination and negative culture for Candida spp. (microbiologic eradication) at the long term follow-up (30 days). The therapeutic cure rate was 67% in the butoconazole group and 61% in the clotrimazole group.

WARNINGS

This cream contains mineral oil. Mineral oil may weaken latex or rubber products such as condoms or vaginal contraceptive diaphragms; therefore, use of such products within 72 hours following treatment with GYNAZOLE•1® Butoconazole Nitrate Vaginal Cream USP, 2% is not recommended.

Recurrent vaginal yeast infections, especially those that are difficult to eradicate, can be an early sign of infection with the human immunodeficiency virus (HIV) in women who are considered at risk for HIV infection.

PRECAUTIONS

General -

If clinical symptoms persist, tests should be repeated to rule out other pathogens, to confirm the original diagnosis, and to rule out other conditions that may predispose a patient to recurrent vaginal fungal infections.

Carcinogenesis, Mutagenesis, Impairment of Fertility -

Carcinogenesis - Long term studies in animals have not been performed to evaluate the carcinogenic potential of this drug.

Mutagenicity - Butoconazole nitrate was not mutagenic when tested in the Ames bacterial test, yeast, chromosomal aberration assay in CHO cells, CHO/HGPRT point mutation assay, mouse micronucleus, and rat dominant lethal assays.

Impairment of Fertility - No impairment of fertility was seen in rabbits or rats administered butoconazole nitrate in oral doses up to 30 mg/kg/day (5 times the human dose based on mg/m^2) or 100 mg/kg/day (10 times the human dose based on mg/m^2), respectively.

Pregnancy Category C -

In pregnant rats administered 6 mg/kg/day of butoconazole nitrate intravaginally during the period of organogenesis, there was an increase in resorption rate and decrease in litter size; however, no teratogenicity was noted. This dose represents a 130- to 353-fold margin of safety based on serum levels achieved in rats following intravaginal administration compared to the serum levels achieved in humans following intravaginal administration of the recommended therapeutic dose of butoconazole nitrate.

Butoconazole nitrate has no apparent adverse effect when administered orally to pregnant rats throughout organogenesis at dose levels up to 50 mg/kg/day (5 times the human dose based on mg/m^2). Daily oral doses of 100, 300 or 750 mg/kg/day (10, 30 or 75 times the human dose based on mg/m^2 respectively) resulted in fetal malformations (abdominal wall defects, cleft palate), but maternal stress was also evident at these higher dose levels. There were, however, no adverse effects on litters of rabbits who received butoconazole nitrate orally, even at maternally stressful dose levels (e.g., 150 mg/kg, 24 times the human dose based on mg/m^2).

Butoconazole nitrate, like other azole antifungal agents, causes dystocia in rats when treatment is extended through parturition. However, this effect was not apparent in rabbits treated with as much as 100 mg/kg/day orally (16 times the human dose based on mg/m^2).

There are, however, no adequate and well-controlled studies in pregnant women. GYNAZOLE • 1® Butoconazole Nitrate Vaginal Cream USP, 2% should be used during pregnancy only if the potential benefit justifies the potential risk to the fetus.

Nursing Mothers -

It is not known whether this drug is excreted in human milk. Because many drugs are excreted in human milk, caution should be exercised when butoconazole nitrate is administered to a nursing woman.

Pediatric Use -

Safety and effectiveness in children have not been established.

ADVERSE REACTIONS

Of the 314 patients treated with GYNAZOLE • 1® Butoconazole Nitrate Vaginal Cream USP, 2% for 1 day in controlled clinical trials, 18 patients (5.7%) reported complaints such as vulvar/vaginal burning, itching, soreness and swelling, pelvic or abdominal pain or cramping, or a combination of two or more of these symptoms. In 3 patients (1%) these complaints were considered treatment-related. Five of the 18 patients reporting adverse events discontinued the study because of them.

DOSAGE AND ADMINISTRATION

The recommended dose of GYNAZOLE • 1® Butoconazole Nitrate Vaginal Cream USP, 2% is one applicatorful of cream (approximately 5 grams of the cream) intravaginally. This amount of cream contains approximately 100 mg of butoconazole nitrate.

HOW SUPPLIED

GYNAZOLE•1® Butoconazole Nitrate Vaginal Cream USP, 2% is available in cartons containing one single-dose prefilled disposable applicator (NDC 45802-396-01).

Store at 25°C (77°F); excursions permitted to 15°-30°C (59°-86°F) [see USP Controlled Room Temperature].

Avoid heat above 30°C (86°F).

Manufactured By Padagis

Yeruham, Israel

Distributed By

PadagisTM

Allegan, MI 49010 • www.padagis.com

Rev 05-22

8F200 RC J2

Patient Package Insert

GYNAZOLE•1®

Butoconazole Nitrate Vaginal Cream USP, 2%

IN ONE PREFILLED DISPOSABLE APPLICATOR

Using the GYNAZOLE•1® Butoconazole Nitrate Vaginal Cream USP, 2%

Prefilled Disposable Applicator

3 Easy Steps:

Step 1: Preparing the Applicator

Peel back the protective foil and remove the prefilled applicator. Applicator is designed to be used with tip in place. Do not remove tip; do not use applicator if tip has been removed.

Do not warm applicator before using. While holding the applicator firmly, pull the ring back to fully extend the plunger (see Figures 1 and 2).

Step 2: Inserting the Applicator

Gently insert the applicator into the vagina as far as it will comfortably go (see Figures 3A and 3B).

Step 3: Applying the Cream

Push the plunger to release the cream (see Figures 4A, 4B and 4C). Remove the empty applicator from the vagina and throw it away.

Important Instructions

- One prefilled applicator of GYNAZOLE • 1® Butoconazole Nitrate Vaginal Cream USP, 2% should be administered.
- This cream contains mineral oil. Mineral oil may weaken latex or rubber products such as condoms or vaginal contraceptive diaphragms; therefore, use of such products within 72 hours following treatment with GYNAZOLE • 1® Butoconazole Nitrate Vaginal Cream USP, 2% is not recommended.
- There are no adequate and well-controlled studies in pregnant women. GYNAZOLE • 1® Butoconazole Nitrate Vaginal Cream USP, 2% should be used during pregnancy only under the supervision of a physician.

Call your doctor for medical advice about side effects.

You may report side effects to FDA at 1-800-FDA-1088.

Manufactured By Padagis

Yeruham, Israel

Distributed By

PadagisTM

Allegan, MI 49010 • www.padagis.com

Rev 05-22

8F200 RC J2

PACKAGE/LABEL PRINCIPAL DISPLAY PANEL

Rx Only

NDC 45802-396-01

GYNAZOLE•1®

Butoconazole Nitrate Vaginal Cream USP, 2%

The applicator delivers approximately 5 g cream, containing 100 mg butoconazole nitrate.

IN ONE PREFILLED DISPOSABLE APPLICATOR

For Vaginal Use Only.

NET WT 5.8 g

The following image is a placeholder representing the product identifier that is either affixed or imprinted on the drug package label during the packaging operation.